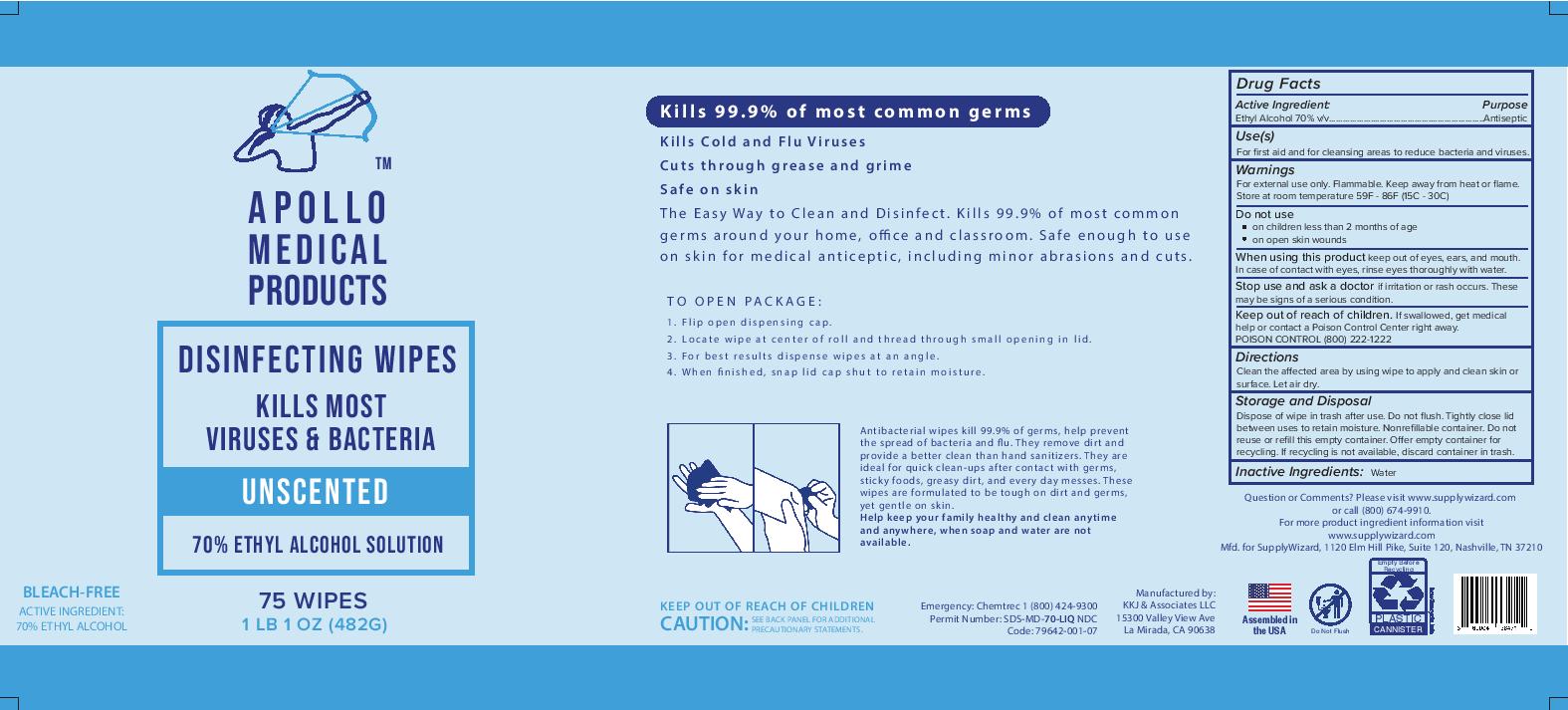 DRUG LABEL: Apollo Medical Products Disinfecting Wipes
NDC: 79642-003 | Form: LIQUID
Manufacturer: KKJ & Associates LLC
Category: otc | Type: HUMAN OTC DRUG LABEL
Date: 20200917

ACTIVE INGREDIENTS: ALCOHOL 70 mL/100 mL
INACTIVE INGREDIENTS: WATER

Apollo Disinfecting Wipes

Active Ingredient(s)

Ethyl Alcohol 70% v/v.

Purpose

Antiseptic

Use

For first aid and for cleansing areas to reduce bacteria and viruses.

Warnings

For external use only. Flammable. Keep away from heat or flame. Store at room temperature 59F-86F (15C-30C)

Do not use

- on children less than 2 months of age
- on open skin wounds

When using this product keep out of eyes, ears, and mouth. In case of contact with eyes, rinse eyes thoroughly with water.

Stop use and ask a doctor if irritation or rash occurs. These may be signs of a serious condition.

Keep out of reach of children. If swallowed, get medical help or contact a Poison Control Center right away. POISON CONTROL (800)-222-1222

Directions

Clean the affected area by using wipe to apply and clean skin or surface. Let air dry.

Other information

- Store between 15-30C (59-86F)
- Avoid freezing and excessive heat above 40C (104F)

Inactive ingredients

Water.

STORAGE AND HANDLING

Dispose of wipe in trash after use. Do not flush. Tightly close lids between uses to retain moisture. Nonrefillable container. Do not reuse or refill this empty container. Offer empty containers for recycling. If recycling is not available, discard container in trash.